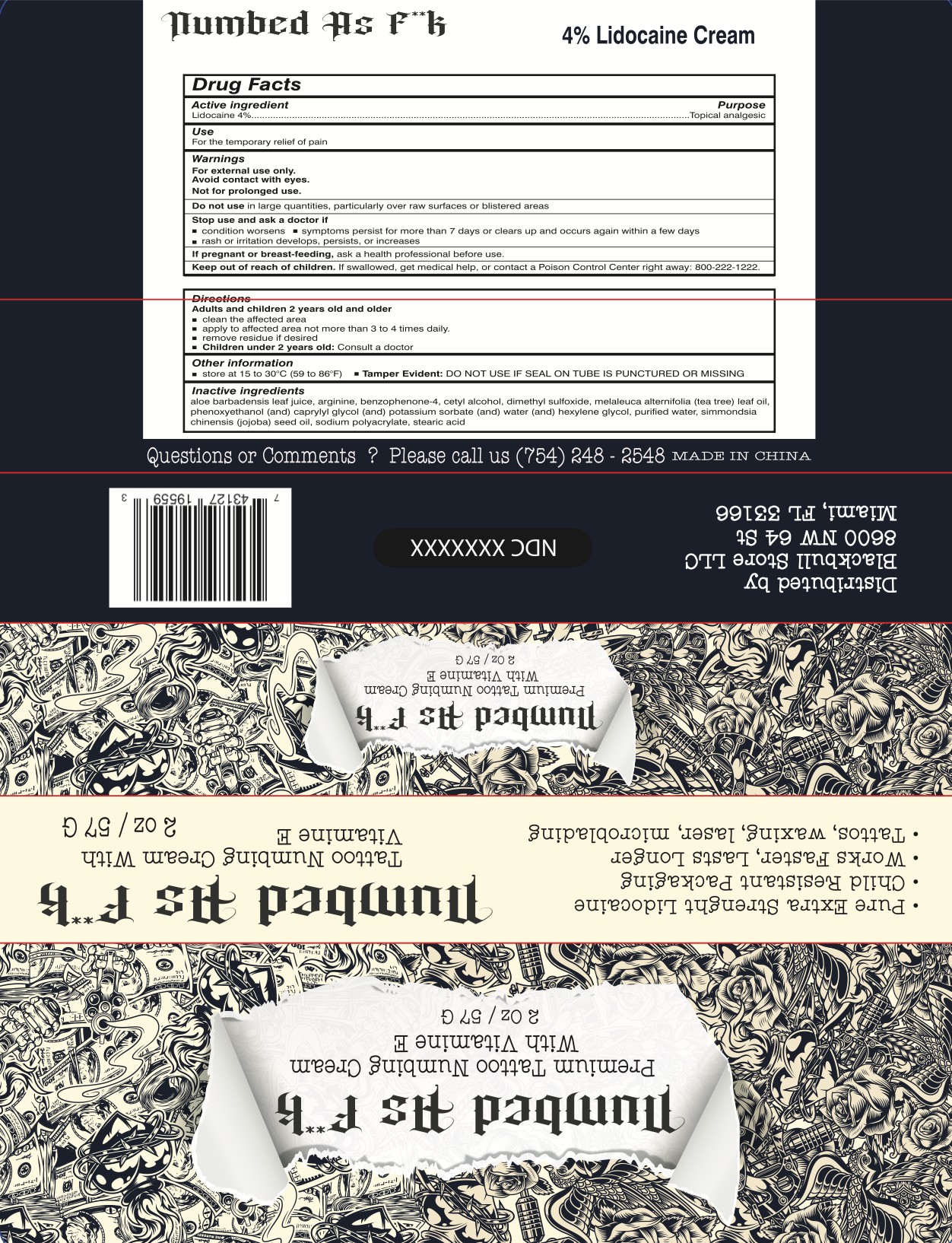 DRUG LABEL: Numbed  As FXXK
NDC: 83371-112 | Form: CREAM
Manufacturer: Blackbull Store LLC
Category: otc | Type: HUMAN OTC DRUG LABEL
Date: 20230709

ACTIVE INGREDIENTS: LIDOCAINE 4 mg/100 mL
INACTIVE INGREDIENTS: STEARETH-21; ISOHEXADECANE; ALCOHOL 95%; PHENOXYETHANOL; CYCLOMETHICONE 5; CETOSTEARYL ALCOHOL; GLYCERYL MONOSTEARATE; .ALPHA.-TOCOPHEROL ACETATE, DL-; HYDROXYETHYL ACRYLATE/SODIUM ACRYLOYLDIMETHYL TAURATE COPOLYMER (45000 MPA.S AT 1%); DIMETHICONE; WATER; ETHYLHEXYLGLYCERIN; DENATONIUM BENZOATE ANHYDROUS; JOJOBA OIL; EDETATE DISODIUM ANHYDROUS; ALOE VERA LEAF; DIHEXADECYL PHOSPHATE; CETETH-10 PHOSPHATE; DIMETHICONE/VINYL DIMETHICONE CROSSPOLYMER (SOFT PARTICLE); MALTODEXTRIN

BlackBull Numbed As FXXK Cream 57 mL

Active Ingredient(s)

Lidocaine 4%

Purpose

Topical Anesthetic

Use

For the temporary relief of pain

Warnings

For external use only.

Avoid contact with eyes.

Not for prolonged use.

Do not use in large quantities, particularly over raw surfaces or blistered areas.

Keep out of reach of children. If swallowed, get medical help, or contact a Poison Control Center right away +1 800-222-1222

Stop Use and Ask a Doctor if the condition worsens ■ symptoms persist for more than seven days or clear up and occur again within a few days. Rash or irritation develops, persists, or increases. If pregnant or breastfeeding, ask a health professional before use.

Directions

Adults and children 2 years old and older Clean the affected area Apply to affected area not more than 3 to 4 times daily Remove residue if desired Children under 2 years old: Consult a doctor

Other information

Store at 15 to 30°C (59 to 86°F) Tamper Evident: DO NOT USE IF SEAL ON TUBE IS PUNCTURED OR MISSING

Inactive ingredients

Acrylates/C10-30 Alkyl Acrylate Crosspolymer, Alcohol, Aloe Barbadensis Leaf Juice, Cetearyl Alcohol, Ceteth-10 Phosphate, Cyclopentasiloxane, Denatonium Benzoate,Dicetyl Phosphate, Dimethicone, Dimethicone/Vinyl Dimethicone Crosspolymer, Disodium EDTA, Ethylhexylglycerin, Gyceryl Stearate, lsohexadecane, Hydroxyethyl Acrylate/Sodium Acryloyldimethyl Taurate Copolymer, Maltodextrin, Phenoxyethanol, Simmondsia Chinensis(Jojoba) Seed Oil, Steareth-21, Tocopheryl Acetate, Water.

QUESTIONS

Call (754) 248 - 2548

Package Label - Principal Display Panel

2 OZ Cream, NDC: 83371-112-11